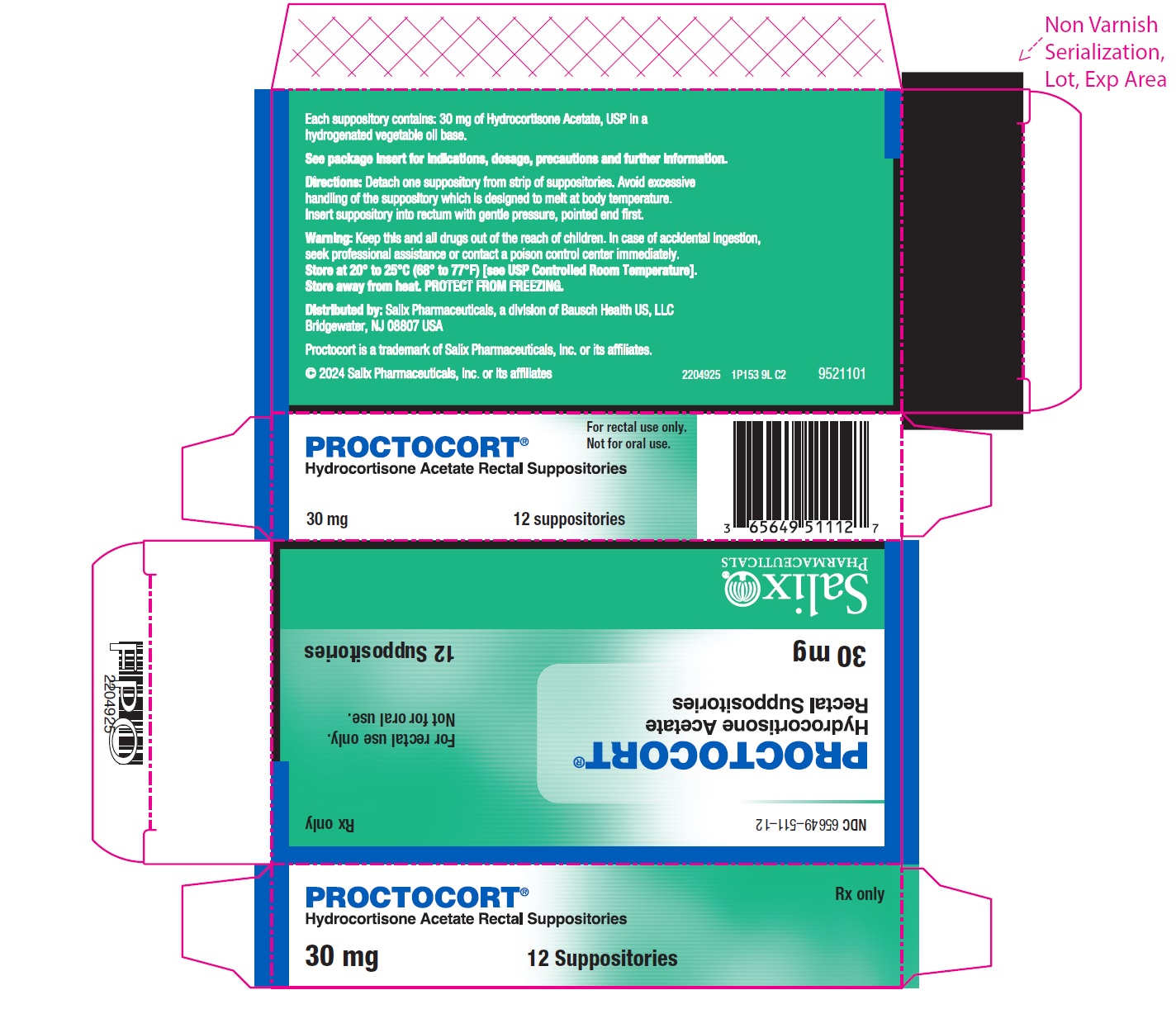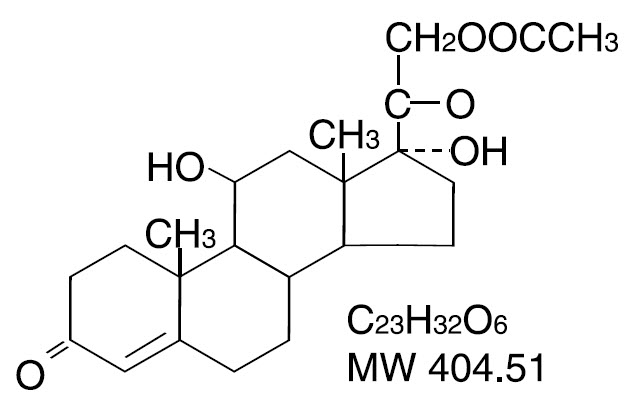 DRUG LABEL: Proctocort
NDC: 65649-511 | Form: SUPPOSITORY
Manufacturer: Salix Pharmaceuticals, Inc
Category: prescription | Type: HUMAN PRESCRIPTION DRUG LABEL
Date: 20240917

ACTIVE INGREDIENTS: HYDROCORTISONE ACETATE 30 mg/1 1
INACTIVE INGREDIENTS: HYDROGENATED PALM OIL; SILICON DIOXIDE; BUTYLATED HYDROXYANISOLE

PROCTOCORT®
Hydrocortisone Acetate Rectal Suppositories, 30 mg
Rx only

DESCRIPTION

Hydrocortisone Acetate is a corticosteroid designated chemically as pregn-4-ene-3, 20-dione, 21-(acetyloxy)-11, 17-dihydroxy-(11β) with the following structural formula:

Each rectal suppository contains hydrocortisone acetate, USP 30 mg in a specially blended hydrogenated vegetable oil base.

CLINICAL PHARMACOLOGY

In normal subjects, about 26% of hydrocortisone acetate is absorbed when the suppository is applied to the rectum. Absorption of hydrocortisone acetate may vary across abraded or inflamed surfaces. Topical steroids are primarily effective because of their anti-inflammatory, anti-pruritic and vasoconstrictive action.

INDICATIONS AND USAGE

Proctocort®Suppositories are indicated for use in inflamed hemorrhoids, postirradiation (factitial) proctitis; as an adjunct in the treatment of chronic ulcerative colitis; cryptitis; and other inflammatory conditions of anorectum and pruritus ani.

CONTRAINDICATIONS

Proctocort®Suppositories are contraindicated in those patients having a history of hypersensitivity to hydrocortisone acetate or any of the components.

PRECAUTIONS

Do not use Proctocort®Suppositories unless adequate proctologic examination is made.

If irritation develops, the product should be discontinued and appropriate therapy instituted.

In the presence of an infection, the use of an appropriate antifungal or anti-bacterial agent should be instituted. If a favorable response does not occur promptly, Proctocort®Suppositories should be discontinued until the infection has been adequately controlled.

Carcinogenesis: No long term studies in animals have been performed to evaluate the carcinogenic potential of corticosteroid suppositories.

Pregnancy Category C: In laboratory animals, topical steroids have been associated with an increase in the incidence of fetal abnormalities when gestating females have been exposed to rather low dosage levels. There are no adequate and well controlled studies in pregnant women. Proctocort®Suppositories should only be used during pregnancy if the potential benefit justifies the risk to the fetus. Drugs of this class should not be used extensively on pregnant patients, in large amounts, or for prolonged periods of time.

Nursing Mothers:It is not known whether this drug is excreted in human milk and because many drugs are excreted in human milk and because of the potential for serious adverse reactions in nursing infants from Proctocort®Suppositories, a decision should be made whether to discontinue nursing or to discontinue the drug, taking into account the importance of the drug to the mother.

ADVERSE REACTIONS

The following local adverse reactions have been reported with hydrocortisone acetate suppositories; burning, itching, irritation, dryness, folliculitis, hypopigmentation, allergic contact dermatitis, secondary infection.

To report SUSPECTED ADVERSE REACTIONS, contact Salix Pharmaceuticals at 1-800-321-4576 or FDA at 1-800-FDA-1088 or www.fda.gov/medwatch.

Drug abuse and dependence have not been reported in patients treated with hydrocortisone acetate suppositories.

OVERDOSAGE

If signs and symptoms of systemic overdosage occur, discontinue use.

DOSAGE AND ADMINISTRATION

For rectal administration. Detach one suppository from strip of suppositories. Remove the foil wrapper. Avoid excessive handling of the suppository which is designed to melt at body temperature. Insert suppository into the rectum with gentle pressure, pointed end first. Insert one suppository in the rectum twice daily, morning and night for two weeks, in nonspecific proctitis. In more severe cases, one suppository three times a day or two suppositories twice daily. In factitial proctitis, the recommended duration of therapy is six to eight weeks or less, according to the response of the individual case.

HOW SUPPLIED

Box of 12 suppositories - 30 mg - NDC 65649-511-12

Box of 24 suppositories - 30 mg - NDC 65649-511-24

Store at 20° to 25°C (68° to 77°F) [see USP Controlled Room Temperature]. Store away from heat. PROTECT FROM FREEZING.

Distributed by:Salix Pharmaceuticals, a division of Bausch Health US, LLC, Bridgewater, NJ 08807 USA

Proctocort is a trademark of Salix Pharmaceuticals, Inc. or its affiliates.

© 2024 Salix Pharmaceuticals, Inc. or its affiliates

Rev. 07/2024

9521401

PACKAGE LABEL

PACKAGE LABEL PRINCIPAL DISPLAY PANEL - PROCTOCORT® 30 mg Carton Label

NDC65649-511-12

Rx only

PROCTOCORT®

Hydrocortisone Acetate Rectal Suppositories

For rectal use only.

Not for oral use.

30 mg 12 Suppositories